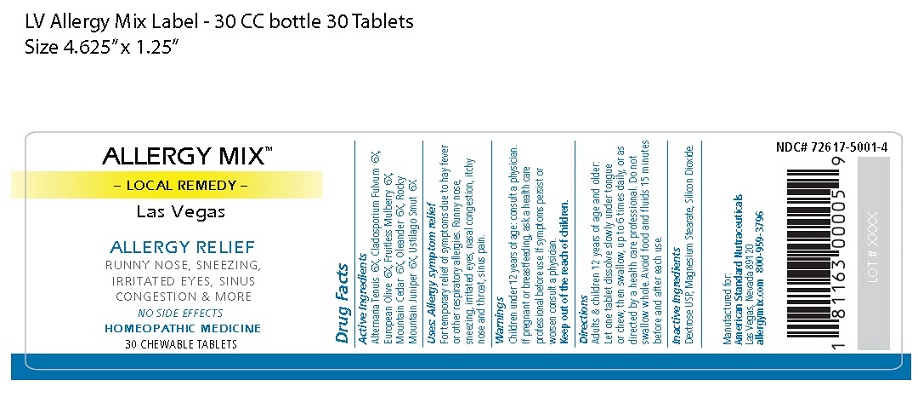 DRUG LABEL: ALLERGY MIX   Las Vegas
NDC: 72617-5001 | Form: TABLET, CHEWABLE
Manufacturer: ASN
Category: homeopathic | Type: HUMAN OTC DRUG LABEL
Date: 20190211

ACTIVE INGREDIENTS: ALTERNARIA ALTERNATA 6 [hp_X]/1 1; PASSALORA FULVA 6 [hp_X]/1 1; OLEA EUROPAEA FLOWER 6 [hp_X]/1 1; WHITE MULBERRY 6 [hp_X]/1 1; JUNIPERUS ASHEI POLLEN 6 [hp_X]/1 1; NERIUM OLEANDER FLOWER 6 [hp_X]/1 1; JUNIPERUS SCOPULORUM POLLEN 6 [hp_X]/1 1; USTILAGO MAYDIS 6 [hp_X]/1 1
INACTIVE INGREDIENTS: DEXTROSE; MAGNESIUM STEARATE; SILICON DIOXIDE

ALLERGY MIX Las Vegas

Active Ingredients
Alternaria Tenuis 6X, Cladosporium Fulvum 6X,
European Olive 6X, Fruitless Mulberry 6X,
Mountain Cedar 6X, Oleander 6X, Rocky
Mountain Juniper 6X, Ustilago Smut 6X

Purpose

Allergy symptom relief

INDICATIONS AND USAGE

Uses: Allergy symptom relief
For temporary relief of symptoms due to hay fever
or other respiratory allergies. Runny nose,
sneezing, irritated eyes, nasal congestion, itchy
nose and throat, sinus pain.

Warnings
Children under 12 years of age: consult a physician.
If pregnant or breastfeeding, ask a health care
professional before use. If symptoms persist or
worsen consult a physician.

Keep out of the reach of children.

Directions
Adults & children 12 years of age and older:
Let one tablet dissolve slowly under tongue or
chew, then swallow, up to 6 times daily, or as
directed by a health care professional. Do not
swallow whole. Avoid food and fluids 15 minutes
before and after each use.

Inactive Ingredients
Dextrose USP, Magnesium Stearate, Silicon Dioxide.

Principal Display Package

ALLERGY MIX™
– LOCAL REMEDY –
Las Vegas

ALLERGY RELIEF

RUNNY NOSE, SNEEZING,
IRRITATED EYES, SINUS
CONGESTION & MORE

NO SIDE EFFECTS

HOMEOPATHIC MEDICINE

30 CHEWABLE TABLETS

NDC# 72617-5001-4

Manufactured for:
American Standard Nutraceuticals
Las Vegas, Nevada 89120
allergymix.com 800-959-3796

1 81163 00005 9

LOT # XXXX

res